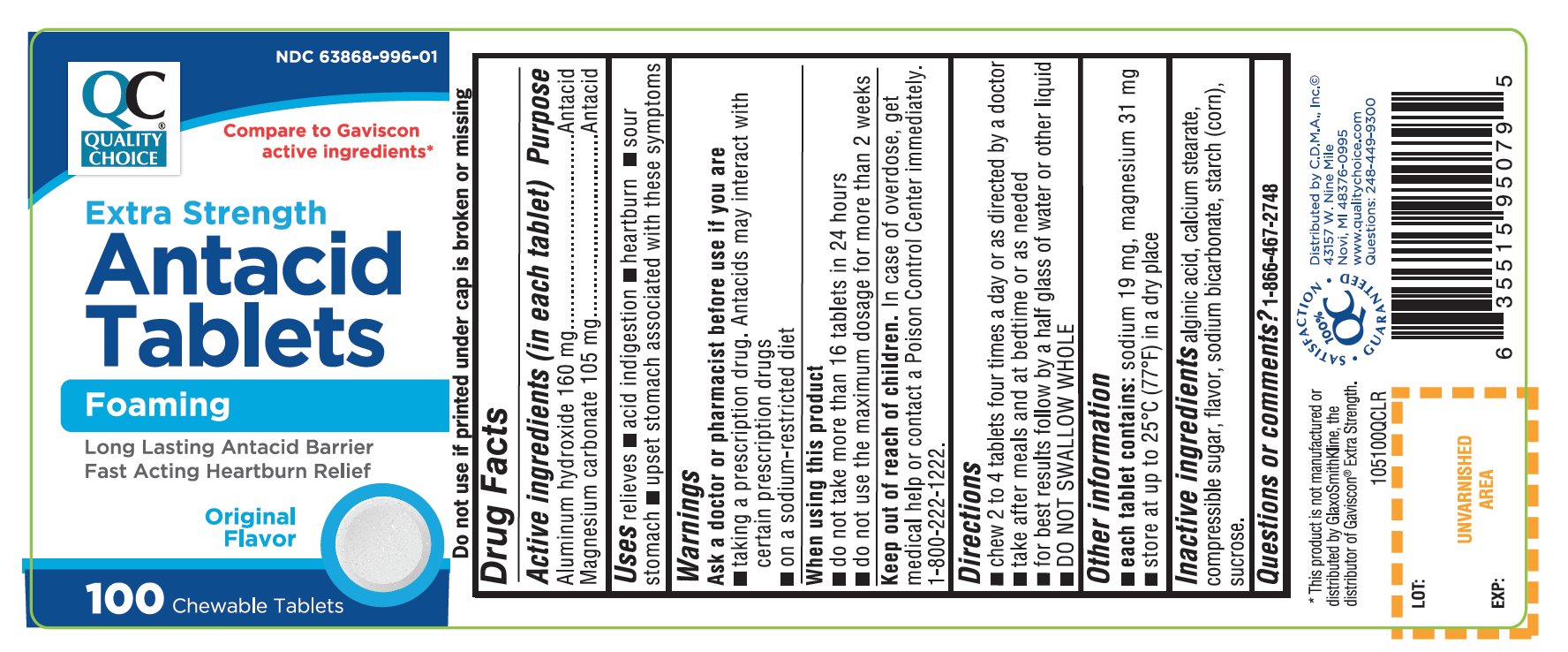 DRUG LABEL: QUALITY CHOICE

NDC: 83324-219 | Form: TABLET, CHEWABLE
Manufacturer: CHAIN DRUG MARKETING ASSOCIATION INC.
Category: otc | Type: HUMAN OTC DRUG LABEL
Date: 20251204

ACTIVE INGREDIENTS: ALUMINUM HYDROXIDE 160 mg/1 1; MAGNESIUM CARBONATE 105 mg/1 1
INACTIVE INGREDIENTS: ALGINIC ACID; CALCIUM STEARATE; CORN SYRUP; SODIUM BICARBONATE; STARCH, CORN; SUCROSE

Quality Choice Antacid Tablets Extra Strength Original Flavor

Active ingredients (in each tablet)

Aluminum hydroxide 160 mg

Magnesium carbonate 105 mg

Purpose

Antacid

Antacid

Uses

- relieves

- acid indigestion
- heartburn
- sour stomach
- upset stomach associated with these symptoms

Warnings

Ask a doctor or pharmacist before use if you are

- taking a prescription drug. Antacids may interact with certain prescription drugs
- If you are on a sodium-restricted diet

When using this product

- do not take more than 16 tablets in 24 hours
- do not use the maximum dosage for more than 2 weeks

Keep out of reach of children.

In case of overdose, get medical help or contact a Poison Control Center immediately at 1-800-222-1222

Directions

- chew 2 to 4 tablets four times a day or as directed by a doctor
- take after meals and at bedtime or as needed
- for best results follow by a half glass of water or other liquid
- DO NOT SWALLOW TABLETS WHOLE

Other information

- each tablet contains:magnesium 31 mg, sodium 19 mg
- Store at room temperature

Inactive ingredients

alginic acid, calcium stearate, compressible sugar, flavor, sodium bicarbonate, starch (corn), sucrose.

Questions or comments

1-866-467-2748

Principal Display Panel

QUALITY CHOICE®

NDC 83324-219-01

Compare to the active ingredients in Gaviscon® Extra Strength Antacid*

Antacid Tablets

Extra Strength

Fast Acting Heartburn Relief

Helps Keep Acid Down For Hours

Original Flavor

100 Chewable Tablets

100% QC SATISFACTION GUARANTEED

- DO NOT USE IF PRINTED INNER SEAL UNDER CAP IS BROKEN OR MISSING.
- Distributed by CDMA., Inc.
- Novi, MI 48375
- www.qualitychoice.com
- Questions: 800-935-2362

*This product is not manufactured or distributed by GlaxoSmithKline, the distributor of Gaviscon®Extra Strength Antacid.